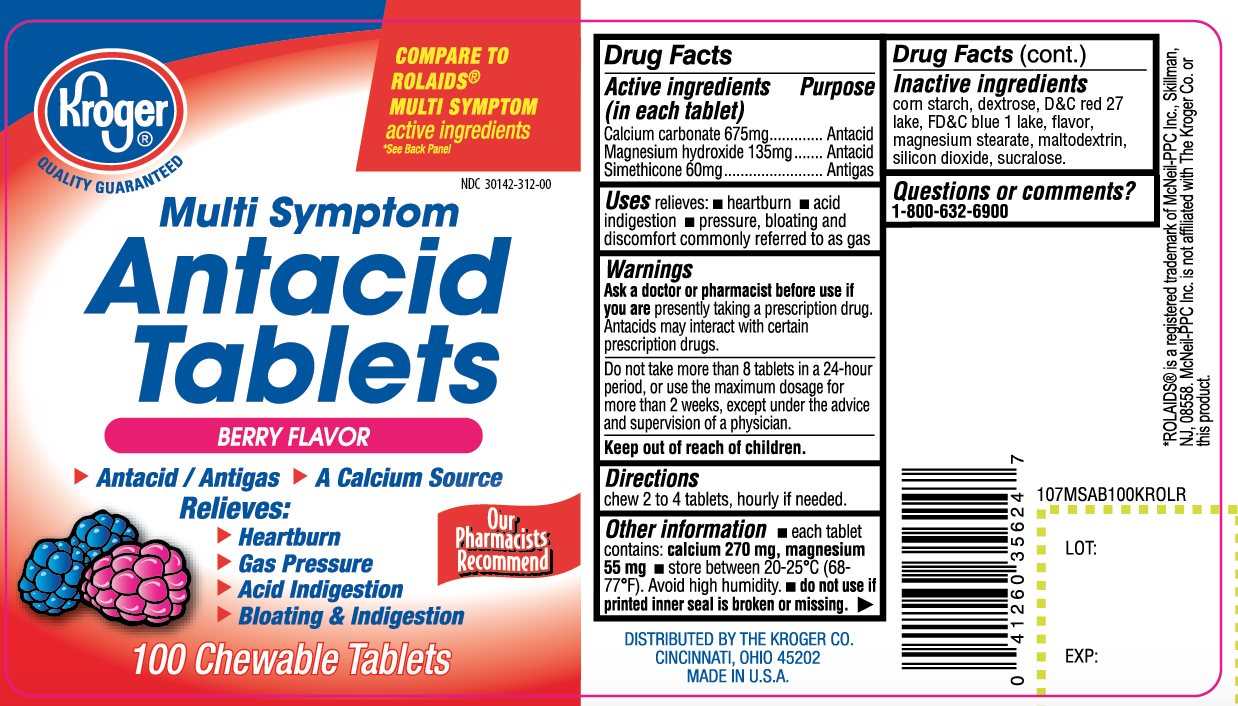 DRUG LABEL: Kroger Multi Symptom
NDC: 30142-312 | Form: TABLET, CHEWABLE
Manufacturer: KROGER COMPANY
Category: otc | Type: HUMAN OTC DRUG LABEL
Date: 20201019

ACTIVE INGREDIENTS: CALCIUM CARBONATE 675 mg/1 1; MAGNESIUM HYDROXIDE 135 mg/1 1; DIMETHICONE 60 mg/1 1
INACTIVE INGREDIENTS: STARCH, CORN; DEXTROSE, UNSPECIFIED FORM; D&C RED NO. 27; FD&C BLUE NO. 1; MAGNESIUM STEARATE; MALTODEXTRIN; SILICON DIOXIDE; SUCRALOSE

Kroger Multi Symptom 100 Chewable Tablets Berry Flavor

Drug Facts

Active ingredients (in each tablet)

Calcium Carbonate USP 675 mg
Magnesium hydroxide USP 135 mg

Simethicone USP 60mg

Purpose

Antacid

Antacid

Antigas

Uses

relieves:

- heartburn
- acid indigestion
- pressure, bloating and discomfort commonly referred to as gas

Warnings

Ask a doctor or pharmacist before use if you are

now taking a prescription drug. Antacids may interact with certain prescription drugs.

When using this product

- Do not take more than 8 tablets in a 24-hour period or use the maximum dosage for more than 2 weeks, except under the advice and supervision of a physician.

Directions

- chew 2-4 tablets, hourly if needed.

Other information

- each tablet contains: calcium 270 mg, magnesium 55 mg
- Store between 20-25°C (68-77°F). Avoid high humidity
- Do not use if printed seal is broken or missing.

Inactive ingredients

corn starch, dextrose, D&C Red 27 lake, FD&C blue 1 lake, flavor, magnesium stearate, maltodextrin, silicon dioxide, sucralose.

Questions or comments?

1-800-632-6900

PRINCIPAL DISPLAY PANEL

NDC# 30142-312-00

COMPARE TO ROLAIDS® MULTI-SYMPTOMS active ingredients

*See Back Panel

Kroger®

QUALITY GUARANTEED

Multi Symptom

Antacid Tablets

BERRY FLAVOR

Antacid/Antigas

A Calcium Source

Relieves:

- Heartburn
- Gas Pressure
- Acid Indigestion
- Bloating & Discomfort

Our Pharmacists Recommend

100 Chewable Tablets

DISTRIBUTED BY THE KROGER CO.

CINCINNATI, OHIO 45202

MADE IN U.S.A

* ROLAIDS® is a registered trademark of McNeil-PPC Inc., Skillman, NJ, 08558. McNeil-PPC Inc. is not affiliated with The Kroger Co. or this product.